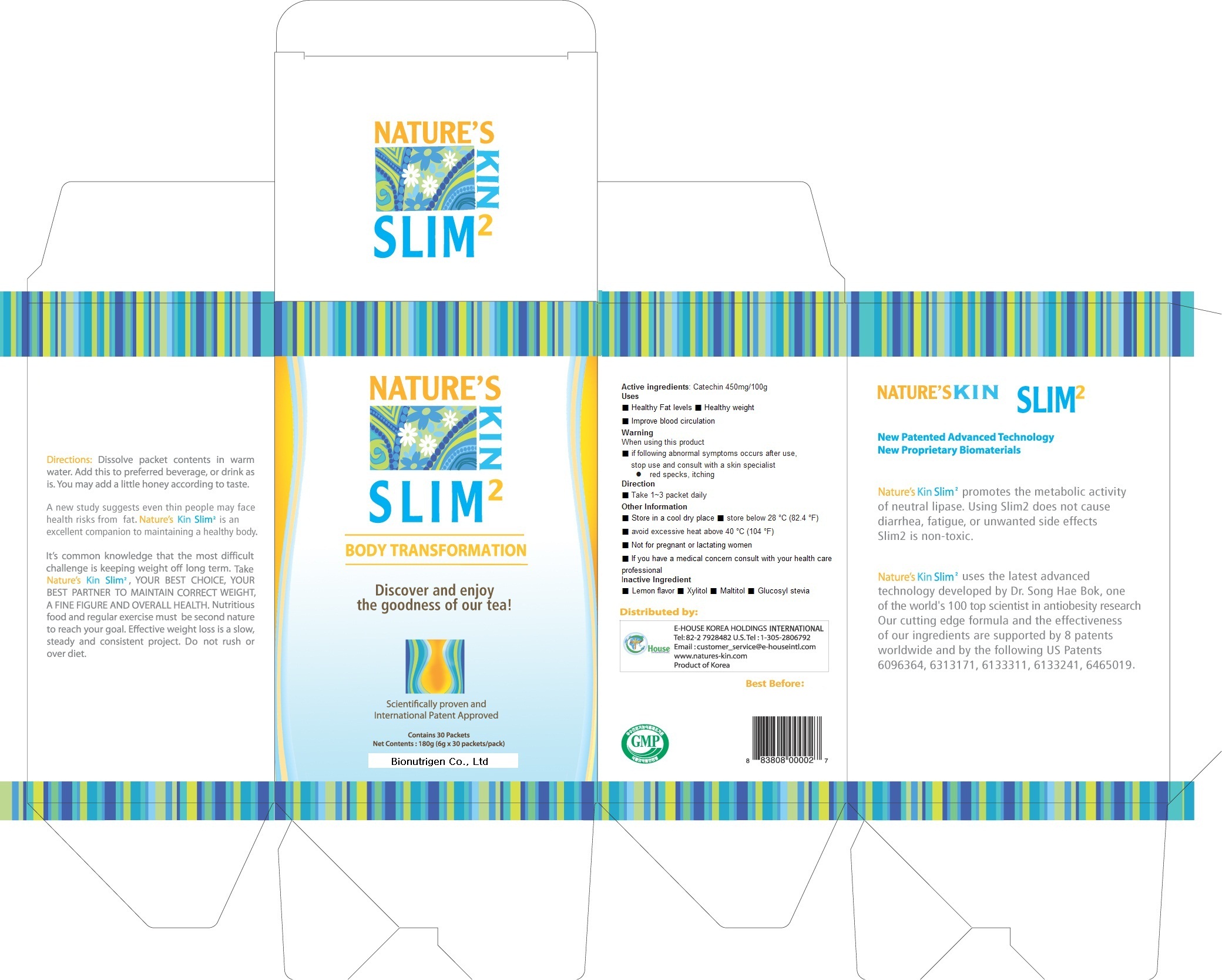 DRUG LABEL: Slim 2
NDC: 60314-1001 | Form: POWDER
Manufacturer: Bionutrigen Co., Ltd.
Category: otc | Type: HUMAN OTC DRUG LABEL
Date: 20110915

ACTIVE INGREDIENTS: CIANIDANOL 0.45 g/100 g
INACTIVE INGREDIENTS: HYDROXYCITRIC ACID; LEMON; XYLITOL; MALTITOL; GLUCOSYL STEVIOL

Drug Facts

active ingredient: catechin

inactive ingredient: HCA, lemon flavor, xylitol, maltitol, glucosyl stevia

PURPOSE

- healthy fat levels
- healthy weight
- improve blood circulation

keep out of reach of the children

INDICATIONS AND USAGE

take 1~3 packet daily

WARNINGS

- store in a cool dry place
- not for pregnant or lactating women

DOSAGE AND ADMINISTRATION

take this medicine before meal